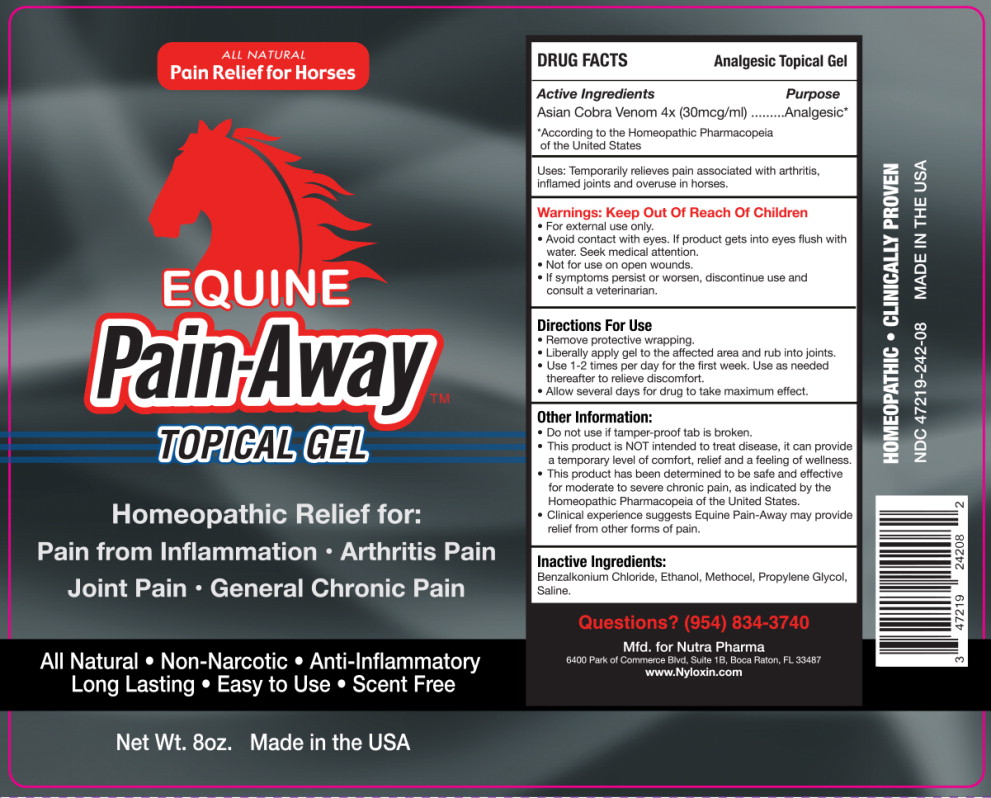 DRUG LABEL: Equine Pain Away
NDC: 47219-242 | Form: GEL
Manufacturer: Nutra Pharma Corporation
Category: homeopathic | Type: OTC ANIMAL DRUG LABEL
Date: 20251014

ACTIVE INGREDIENTS: NAJA NAJA VENOM 4 [hp_X]/1 mL
INACTIVE INGREDIENTS: BENZALKONIUM CHLORIDE; ALCOHOL; CARBOXYMETHYLCELLULOSE SODIUM, UNSPECIFIED; PROPYLENE GLYCOL; ISOTONIC SODIUM CHLORIDE SOLUTION

DRUG FACTS

Analgesic Topical Gel

Active Ingredients

Asian Cobra Venom 4x (30mcg/ml)

Purpose

Analgesic*

*According to the Homeopathic Pharmacopeia of the United States

Uses:

Temporarily relieves joint pain associated with overuse and pain associated with arthritis.

Warnings:

Keep Out Of Reach Of Children

- For external use only.
- Avoid contact with eyes. If product gets into eyes, flush with water. Seek medical attention.
- Not for use on open wounds.
- If symptoms persist or worsen, discontinue use and seek medical attention.

Directions For Use:

- Remove protective wrapping.
- Liberally apply gel to the affected area and rub into joints.
- Use 1-2 times per day for the first week. Use as needed thereafter to relieve discomfort.
- Allow several days for drug to take maximum effect.

Other Information:

- Do not use if tamper-proof tab is broken.
- This product is NOT intended to treat disease, it can provide a temporary level of comfort, relief and a feeling of wellness.
- This product has been determined to be safe and effective for moderate to severe chronic pain, as indicated by the Homeopathic Pharmacopeia of the United States.
- Clinical experience suggests Equine Pain-Away may provide relief from other forms of pain.

Inactive Ingredients:

Benzalkonium Chloride, Ethanol, Methocel, Propylene Glycol, Saline.

Principal Display Panel - 8 oz Carton Label

ALL NATURAL
Pain Relief for Horses

EQUINE
Pain-Away™
TOPICAL GEL

Homeopathic Relief for:
Pain from Inflammation • Arthritis Pain
Joint Pain • General Chronic Pain

All Natural • Non-Narcotic • Anti-Inflammatory
Long Lasting • Easy to Use • Scent Free

Net Wt. 8oz.

Made in the USA